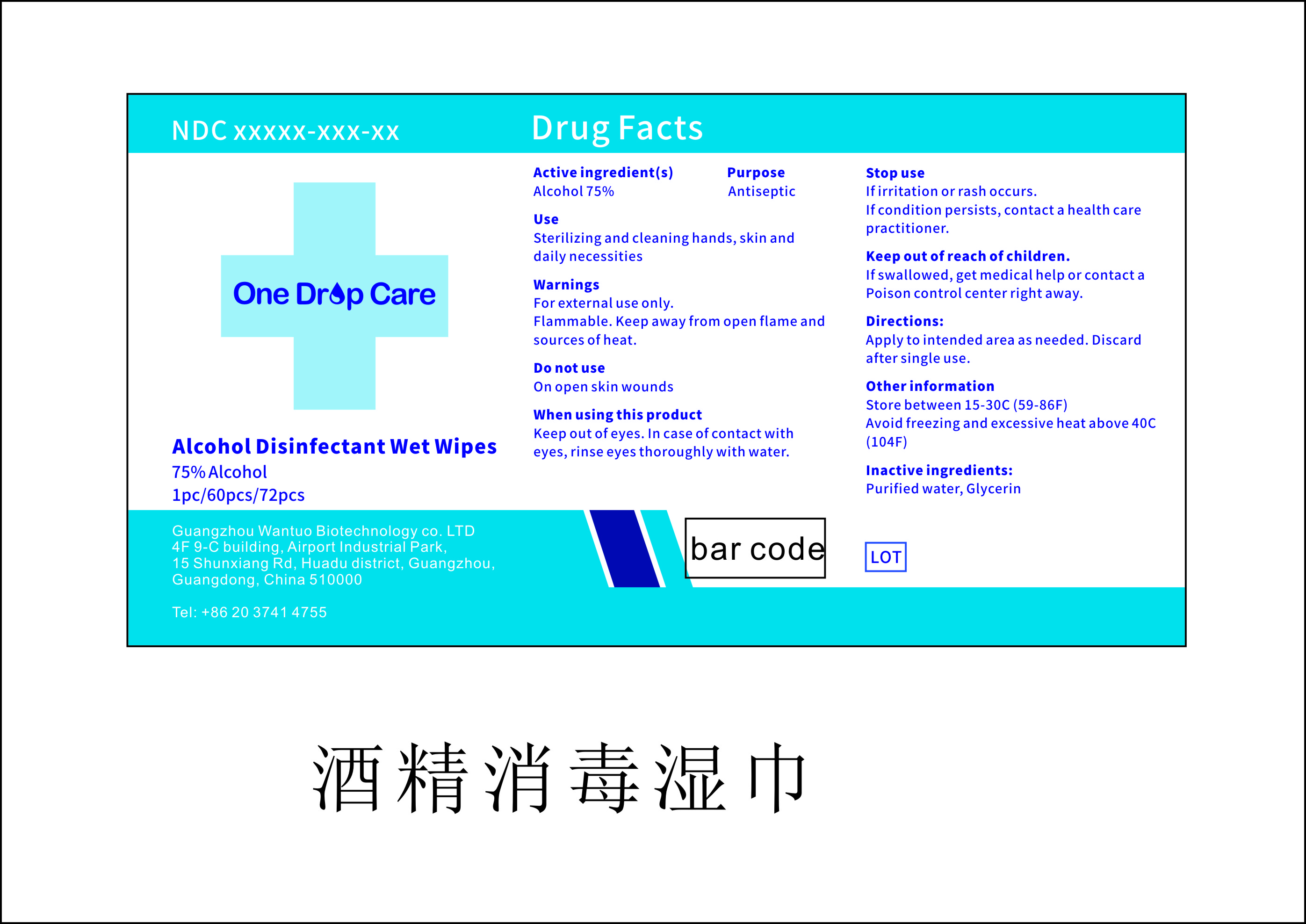 DRUG LABEL: One Drop Care Alcohol Disinfectant Wet Wipes
NDC: 75226-002 | Form: SOLUTION
Manufacturer: Guangzhou Wantuo Biotechnology Co. LTD
Category: otc | Type: HUMAN OTC DRUG LABEL
Date: 20200509

ACTIVE INGREDIENTS: ALCOHOL 2.25 mL/1 1
INACTIVE INGREDIENTS: WATER; GLYCERIN

NA

Active Ingredient(s)

Alcohol 75%

Purpose

Antiseptic

Use

Sterilizing and cleaning hands, skin, and daily necessites

Warnings

For external use only. Flammable. Keep away from open flame and sources of heat

Do not use on open skin wounds

When using this product keep out of eyes, ears, and mouth. In case of contact with eyes, rinse eyes thoroughly with water.

Stop use if irritation or rash occurs. If condition persists contact a healthcare pratitioner

Keep out of reach of children. If swallowed, get medical help or contact a Poison Control Center right away.

Directions

Apply to intended area as needed

Other information

- Store between 15-30C (59-86F)
- Avoid freezing and excessive heat above 40C (104F)

Inactive ingredients

Water